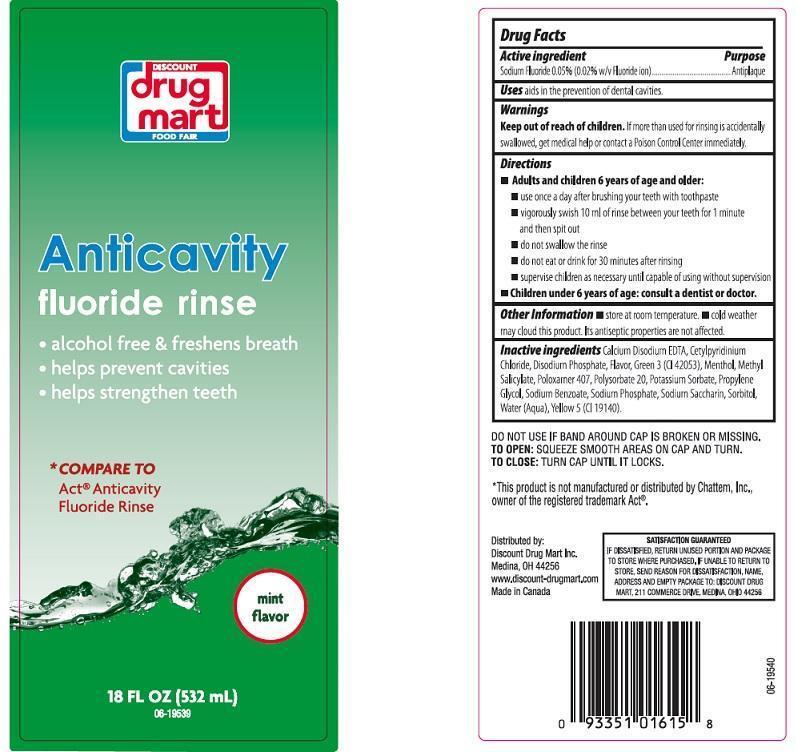 DRUG LABEL: DISCOUNT DRUG MART
NDC: 53943-554 | Form: LIQUID
Manufacturer: DISCOUNT DRUG MART
Category: otc | Type: HUMAN OTC DRUG LABEL
Date: 20140516

ACTIVE INGREDIENTS: SODIUM FLUORIDE 0.5 mg/1 mL
INACTIVE INGREDIENTS: EDETATE CALCIUM DISODIUM; CETYLPYRIDINIUM CHLORIDE; SODIUM PHOSPHATE, DIBASIC, ANHYDROUS; FD&C GREEN NO. 3; MENTHOL; METHYL SALICYLATE; POLOXAMER 407; POLYSORBATE 20; POTASSIUM SORBATE; PROPYLENE GLYCOL; SODIUM BENZOATE; SODIUM PHOSPHATE; SACCHARIN SODIUM; SORBITOL; WATER; FD&C YELLOW NO. 5

DRUG FACTS

ACTIVE INGREDIENT

SODIUM FLUORIDE 0.05% (0.02% W/V FLUORIDE ION)

PURPOSE

ANTIPLAQUE

USES

AIDS IN THE PREVENTION OF DENTAL CAVITIES

WARNINGS

KEEP OUT OF REACH OF CHILDREN

IF MORE THAN USED FOR RINSING IS ACCIDENTALLY SWALLOWED, GET MEDICAL HELP OR CONTACT A POISON CONTROL CENTER IMMEDIATELY

DIRECTIONS

ADULTS AND CHILDREN 6 YEARS OF AGE AND OLDER: USE ONCE A DAY AFTER BRUSHING YOUR TEETH WITH TOOTHPASTE. VIGOROUSLY SWISH 10 ML OF RINSE BETWEEN YOUR TEETH FOR 1 MINUTE AND THEN SPIT OUT. DO NOT SWALLOW THE RINSE. DO NOT EAT OR DRINK FOR 30 MINUTES AFTER RINSING. SUPERVISE CHILDREN AS NECESSARY UNTIL CAPABLE OF USING WITHOUT SUPERVISION. CHILDREN UNDER 6 YEARS OF AGE: CONSULT A DENTIST OR DOCTOR

OTHER INFORMATION

STORE AT ROOM TEMPERATURE. COLD WEATHER MAY CLOUD THIS PRODUCT. ITS ANTISEPTIC PROPERTIES ARE NOT AFFECTED

INACTIVE INGREDIENTS

CALCIUM DISODIUM EDTA, CETYLPYRIDINIUM CHLORIDE, DISODIUM PHOSPHATE, FLAVOR, GREEN 3 (CI 42053), MENTHOL, METHYL SALICYLATE, POLOXAMER 407, POLYSORBATE 20, POTASSIUM SORBATE, PROPYLENE GLYCOL, SODIUM BENZOATE, SODIUM PHOSPHATE, SODIUM SACCHARIN, SORBITOL, WATER (AQUA), YELLOW 5 (CI 19140).